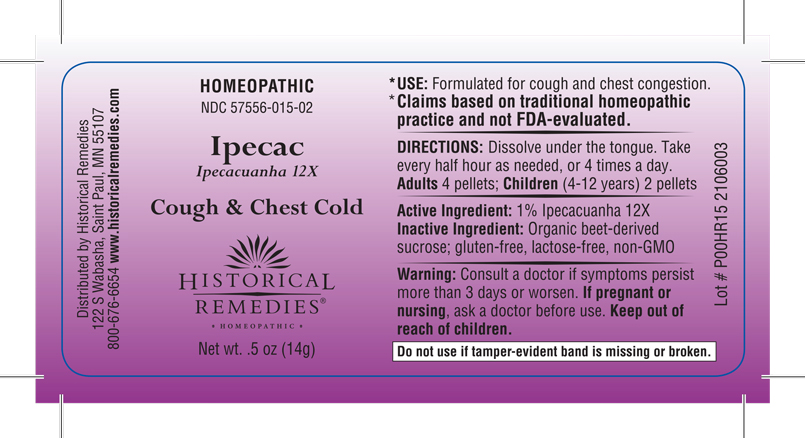 DRUG LABEL: Ipecacuanha
NDC: 57556-015 | Form: PELLET
Manufacturer: Historical Remedies
Category: homeopathic | Type: HUMAN OTC DRUG LABEL
Date: 20251007

ACTIVE INGREDIENTS: IPECAC 12 [hp_X]/1 g
INACTIVE INGREDIENTS: SUCROSE

Ipecac 015P

INDICATIONS & USAGE SECTION

Formulated for cough and chest congestion.

DOSAGE & ADMINISTRATION SECTION

Directions: Adults4 pellets; Children(4-12 years) 2 pellets; Dissolve under the tongue. Take every half hour as needed, or 4 times a day.

OTC - ACTIVE INGREDIENT SECTION

1% Ipecacuanha 12x

OTC - PURPOSE SECTION

Formulated for cough and chest congestion.

INACTIVE INGREDIENT SECTION

Inactive Ingredients: Organic beet-derived sucrose; gluten-free, lactose-free, non-GMO

QUESTIONS SECTION

Distributed by Historical Remedies; 122 S Wabasha, Saint Paul, MN 55107; 800-676-6654

www.historicalremedies.com

WARNINGS SECTION

Warning: Consult a doctor if symptoms persist more than 3 days or worsen. If pregnant or nursing, ask a doctor before use. Keep out of reach of children. Do not use if tamper-evident band is missing or broken.

OTC - PREGNANCY OR BREAST FEEDING SECTION

If pregnant or breast-feeding,ask a doctor before use.

OTC - KEEP OUT OF REACH OF CHILDREN SECTION

Keep out of reach of children.